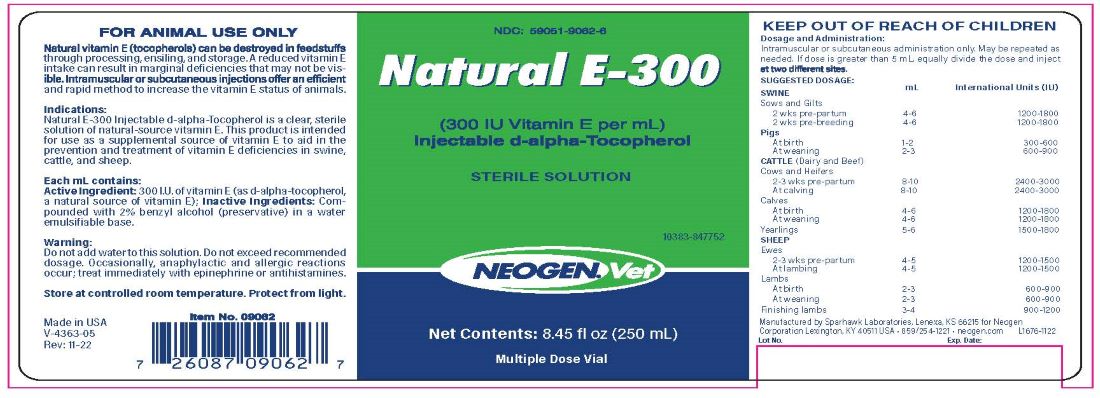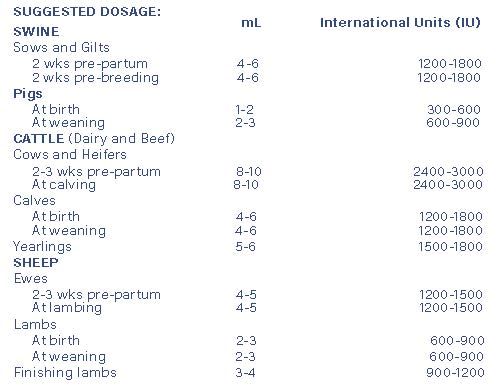 DRUG LABEL: Natural E-300
NDC: 59051-9062 | Form: INJECTION
Manufacturer: Neogen Corporation - Nandino
Category: animal | Type: OTC ANIMAL DRUG LABEL
Date: 20231205

ACTIVE INGREDIENTS: ALPHA-TOCOPHEROL 300 mg/1 mL

Natual E-300

DOSAGE AND ADMINISTRATION

(300 IU vitamin E per mL)

INJECTABLE TOCOPHEROLSTERILE SOLUTION

KEEP OUT OF REACH OF CHILDREN
Dosage and Administration:
Intramuscular or subcutaneous administration only. May be repeated as needed. If dose is greater than 5 mL, equally divide the dose and inject at two different sites.

PURPOSE

FOR ANIMAL USE ONLY

Natural tocopherols in feedstuffs can be destroyed through process, ensiling and storage. A reduced vitamin E intake can result in marginal deficiencies that may not be visible. Intramuscular or subcutaneous injections offer an efficient and rapid method to increase vitamin E status of animals.

INDICATIONS

Vitamin E-300 Injectable Tocopherol (natural-source vitamin E) is a clear, sterile, water emulsifiable solution of d-alpha-tocopherol for use as an aid in the prevention and treatment of vitamin E deficiencies in swine, cattle and sheep. This product is intended as a supplemental source of natural vitamin E.

Each mL contains:

Active Ingredient: 300 I.U. of vitamin E (as d-alpha-tocopherol, a natural source of vitamin E); Inactive Ingredients: Com-pounded with 2% benzyl alcohol (preservative) in a water emulsifiable base.

Warnings:

Do not add water to this solution. Do not exceed recommended dosage. Occasionally, anaphylactic and allergic reactions occur; treat immediately with epinephrine or antihistamines.

STORAGE AND HANDLING

Store at controlled room temperature. Protect from light.